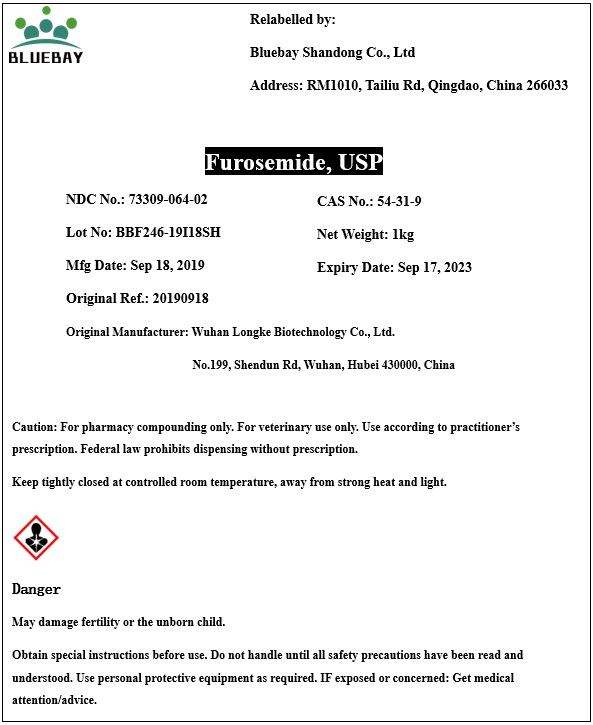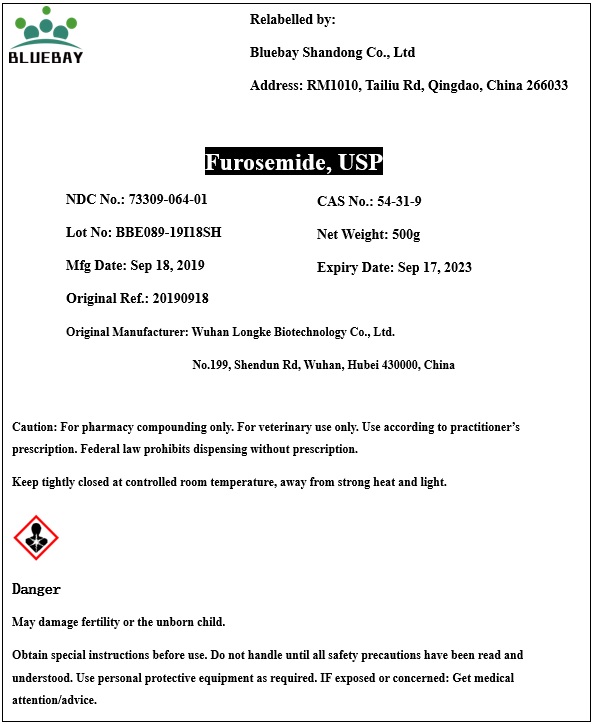 DRUG LABEL: Furosemide
NDC: 73309-064 | Form: POWDER
Manufacturer: BLUEBAY SHANDONG CO.,LTD
Category: other | Type: BULK INGREDIENT
Date: 20200609

ACTIVE INGREDIENTS: FUROSEMIDE 1 g/1 g

Furosemide